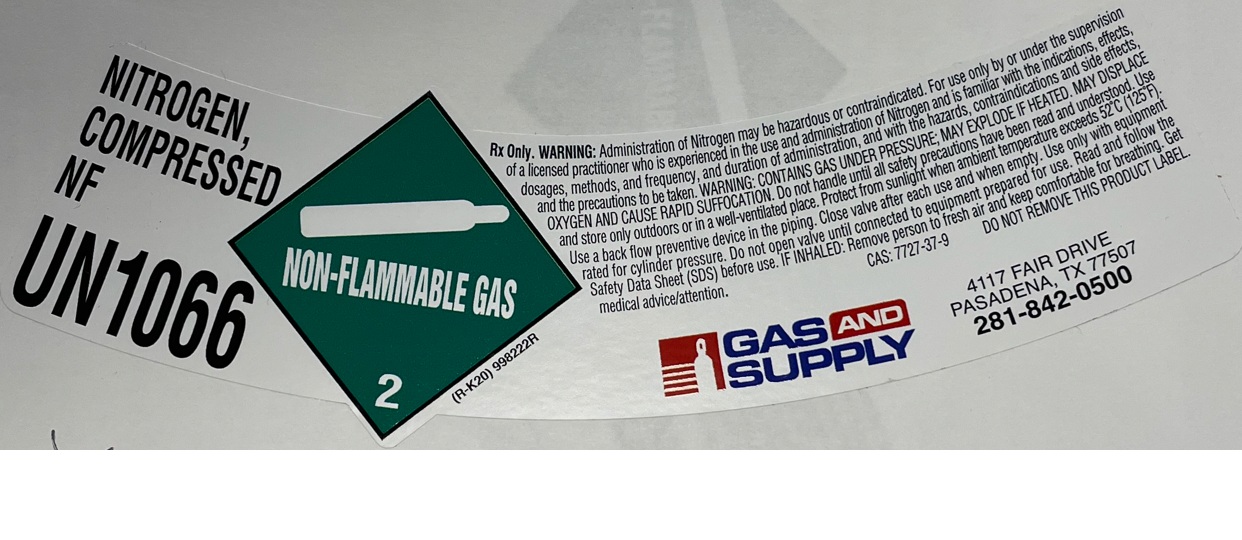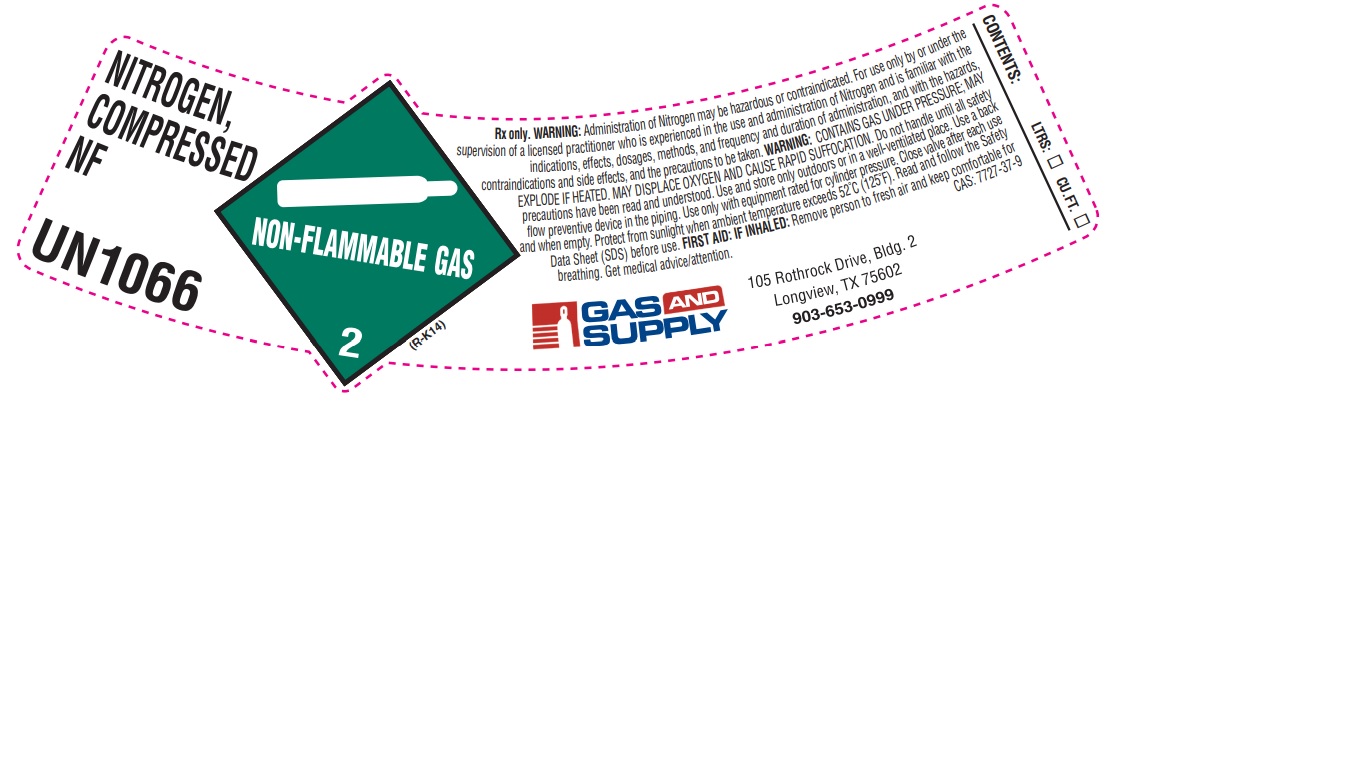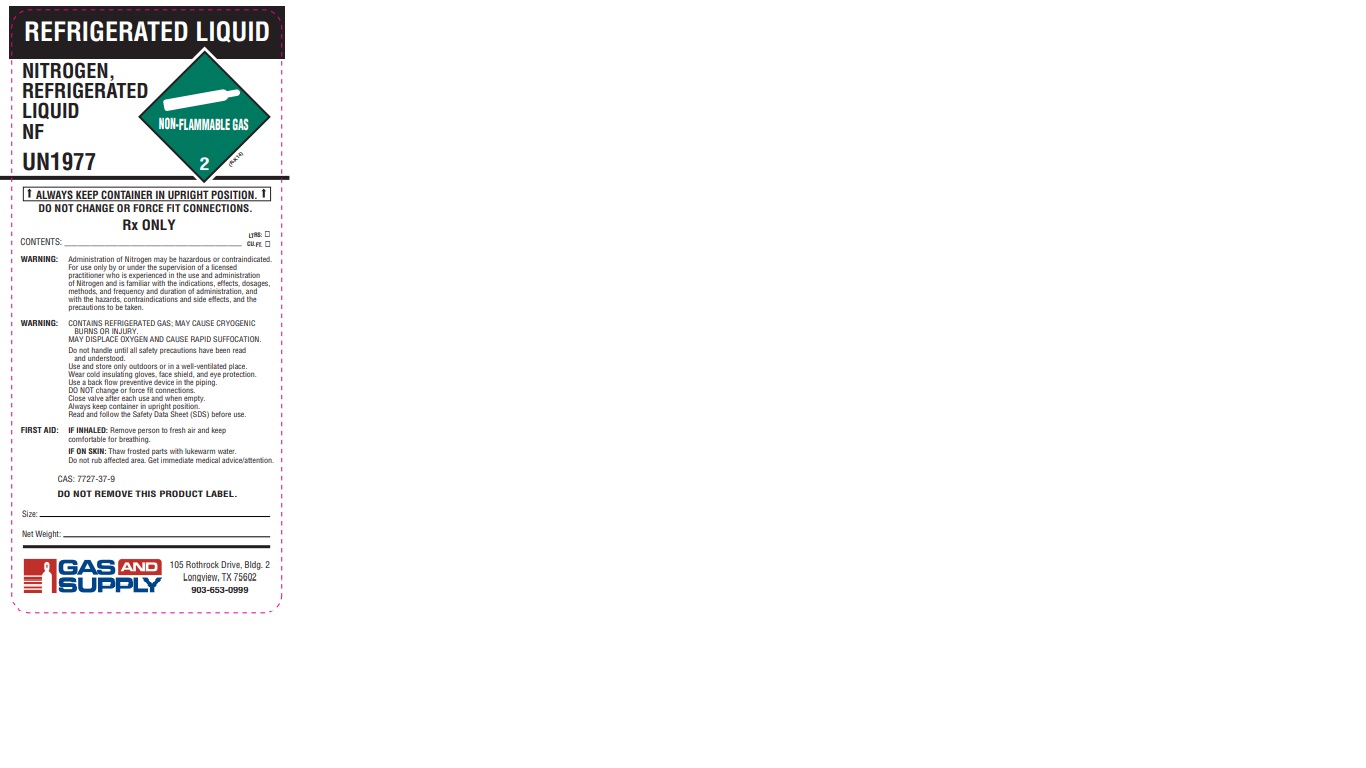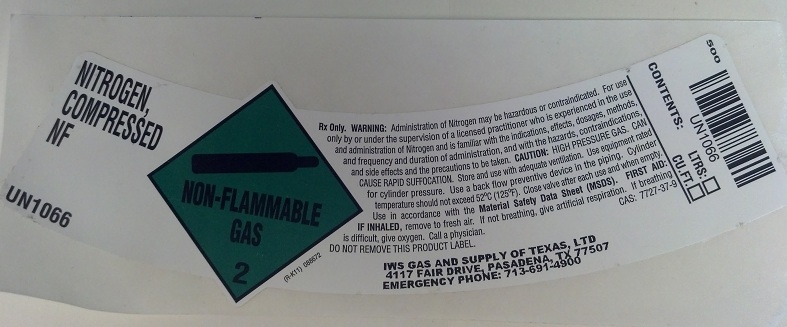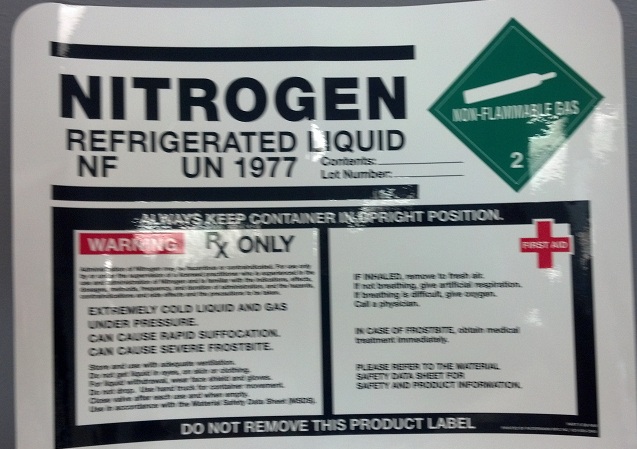 DRUG LABEL: Nitrogen
NDC: 53425-002 | Form: GAS
Manufacturer: IWS Gas and Supply of Texas, LTD
Category: prescription | Type: HUMAN PRESCRIPTION DRUG LABEL
Date: 20251208

ACTIVE INGREDIENTS: NITROGEN 995 mL/1 L

Nitrogen

PACKAGE LABEL

NITROGEN, COMPRESSED NF UN1066

NON-FLAMMABLE GAS 2

Rx ONLY. WARNING: Administration of Nitrogen may be hazardous or contraindicated. For use only by or under the supervision of a licensed practitioner who is experienced in the use and administration of Nitrogen and is familiar with the indications, effects, dosage, methods, and frequency and duration of administration, and with the hazards, contraindications, and side effects and the precautions to be taken. CAUTION: HIGH PRESSURE GAS. CAN CAUSE RAPID SUFFOCATION. Store and use with adequate ventilation. Use equipment rated for cylinder pressure. Use a back flow preventive device in the piping. Cylinder temperature should not exceed 52 degrees C (125 degrees F). Close valve after each use and when empty. Use in accordance with the Material Safety Data Sheet (MSDS). FIRST AID: IF INHALED, remove to fresh air. If not breathing, give artificial respiration. If breathing is difficulty, give oxygen. Call a physician. CAS: 7727-37-9

DO NOT REMOVE THIS PRODUCT LABEL.

IWS GAS AND SUPPLY OF TEXAS, LTD
4117 FAIR DRIVE, PASADENA, TX 77507
EMERGENCY PHONE: 713-691-4900
CONTENTS: LTRS: CU.FT.

UN1066

PACKAGE LABEL

NITROGEN REFRIGERATED LIQUID NF UN1977

Contents: Lot Number: NON-FLAMMABLE 2

ALWAYS KEEP CONTAINER IN UPRIGHT POSITION.

WARNING RX ONLY

Administration of Nitrogen may be hazardous or contraindicated. for use only by or under the supervision of a licensed practitioner who is experienced in the use and administration of Nitrogen and is familiar with the indications, effects, dosages, methods, frequency, and duration of administration, and the hazards, contraindications and side effects and the precautions to be taken.

EXTREMELY COLD LIQUID AND GAS UNDER PRESSURE. CAN CAUSE RAPID SUFFOCATION. CAN CAUSE SEVERE FROSTBITE. Store and use with adequate ventilation. Do not get liquid in eyes, on skin or clothing. For liquid withdrawal, wear face shield and gloves. Do not drop. Use hand truck for container movement. Clove valve after each use and when empty. Use in accordance with the Material Safety Data Sheet (MSDS).

IN INHALED, remove to fresh air. If not breathing, give artificial respiration. If breathing is difficult, give oxygen. Call a physician. IN CASE OF FROSTBITE, obtain medical treatment immediately.

PLEASE REFER TO THE MATERIAL SAFETY DATA SHEET FOR SAFETY AND PRODUCT INFORMATION.

PACKAGE LABEL

NITROGEN, COMPRESSED NF

UN1066

Rx only. WARNING: Administration of Nitrogen may be hazardous or contraindicated. For use only by or under the supervision of a licensed practitioner who is experienced in the use and administration of Nitrogen and is familiar with the indications, effects, methods, and frequency and duration of administration, and with the hazards, contraindications and side effects, and the precautions to be taken. WARNING: CONTAINS GAS UNDER PRESSURE; MAY EXPLODE IF HEATED. MAY DISPLACE OXYGEN AND CAUSE RAPID SUFFOCATION. Do not handle until all safety precautions have been read and understood. Use and store only outdoors or in a well-ventilated place. Use a back flow preventive device in the piping. Use only with equipment rated for cylinder pressure. Close valve after each use and when empty. Protect from sunlight when ambient temperature exceeds 52 C (125 F). Read and follow the Safety Data Sheet (SDS) before use. FIRST AID: IF INHALED: Remove person to fresh air and keep comfortable for breathing. Get medical advice/attention. CAS: 7727-37-9

GAS AND SUPPLY

105 Rothrock Drive, Bldg. 2

Longview, TX 75602

903-653-0999

CONTENTS: LTRS: CU.FT.

PACKAGE LABEL

REFRIGERATED LIQUID

NITROGEN, REFRIGERATED LIQUID NF

UN1977

ALWAYS KEEP CONTAINER IN UPRIGHT POSITION.

DO NOT CHANGE OR FORCE FIT CONNECTIONS.

Rx ONLY

CONTENTS: LTRS: CU.FT.

WARNING: Administration of Nitrogen may be hazardous or contraindicated. For use only by or under the supervision of a licensed practitioner who is experienced in the use and administration of Nitrogen and is familiar with the indications, effects, dosages, methods, and frequency and duration of administration, and with the hazards, contraindications and side effects, and the precautions to be taken.

WARNING: CONTAINS REFRIGERATED GAS; MAY CAUSE CRYOGENIC BURNS OR INJURY. MAY DISPLACE OXYGEN AND CAUSE RAPID SUFFOCATION.

Do not handle until all safety precautions have been read and understood. Use and store only outdoors or in a well-ventilated place. Wear cold insulating gloves, face shield, and eye protection. Use a back flow preventive device in the piping. DO NOT change or force fit connections. Close valve after each use and when empty. Always keep container in upright position. Read and follow the Safety Data Sheet (SDS) before use.

FIRST AID: IF INHALED: Remove person to fresh air and keep comfortable for breathing.

IF ON SKIN: Thaw frosted parts with lukewarm water. Do not rub affected area. Get immediate medical advice/attention.

CAS: 7727-37-9

DO NOT REMOVE THIS PRODUCT LABEL.

Size:

Net Weight:

GAS AND SUPPLY

105 Rothrock Drive, Bldg. 2

Longview, TX 75602

903-653-0999

PACKAGE LABEL

NITROGEN, COMPRESSED NF

UN1066

Rx Only. WARNING: Administration of Nitrogen may be hazardous or contraindicated. For use only by or under the supervision of a licensed practitioner who is experienced in the use and administration of Nitrogen and is familiar with the indications, effects, dosages, methods, and frequency, and duration of administration, and with the hazards, contraindications and side effects, and the precautions to be taken. WARNING: CONTAINS GAS UNDER PRESSURE; MAY EXPLODE IF HEATED. MAY DISPLACE OXYGEN AND CAUSE RAPID SUFFOCATION. Do not handle until all safety precautions have been read and understood. Use and store only outdoors or in a well-ventilated place. Protect from sunlight when ambient temperature exceeds 52 C (125 F). Use a back flow preventive device in the piping. Close valve after each use and when empty. Use only with equipment rated for cylinder pressure. Do not open valve until connected to equipment prepared for use. Read and follow the Safety Data Sheet (SDS) before use. IF INHALED: Remove person to fresh air and keep comfortable for breathing. Get medical advice/attention.

CAS: 7727-37-9 DO NOT REMOVE THIS PRODUCT LABEL.

GAS AND SUPPLY

117 FAIR DRIVE

PASADENA, TX 77507

281-842-0500